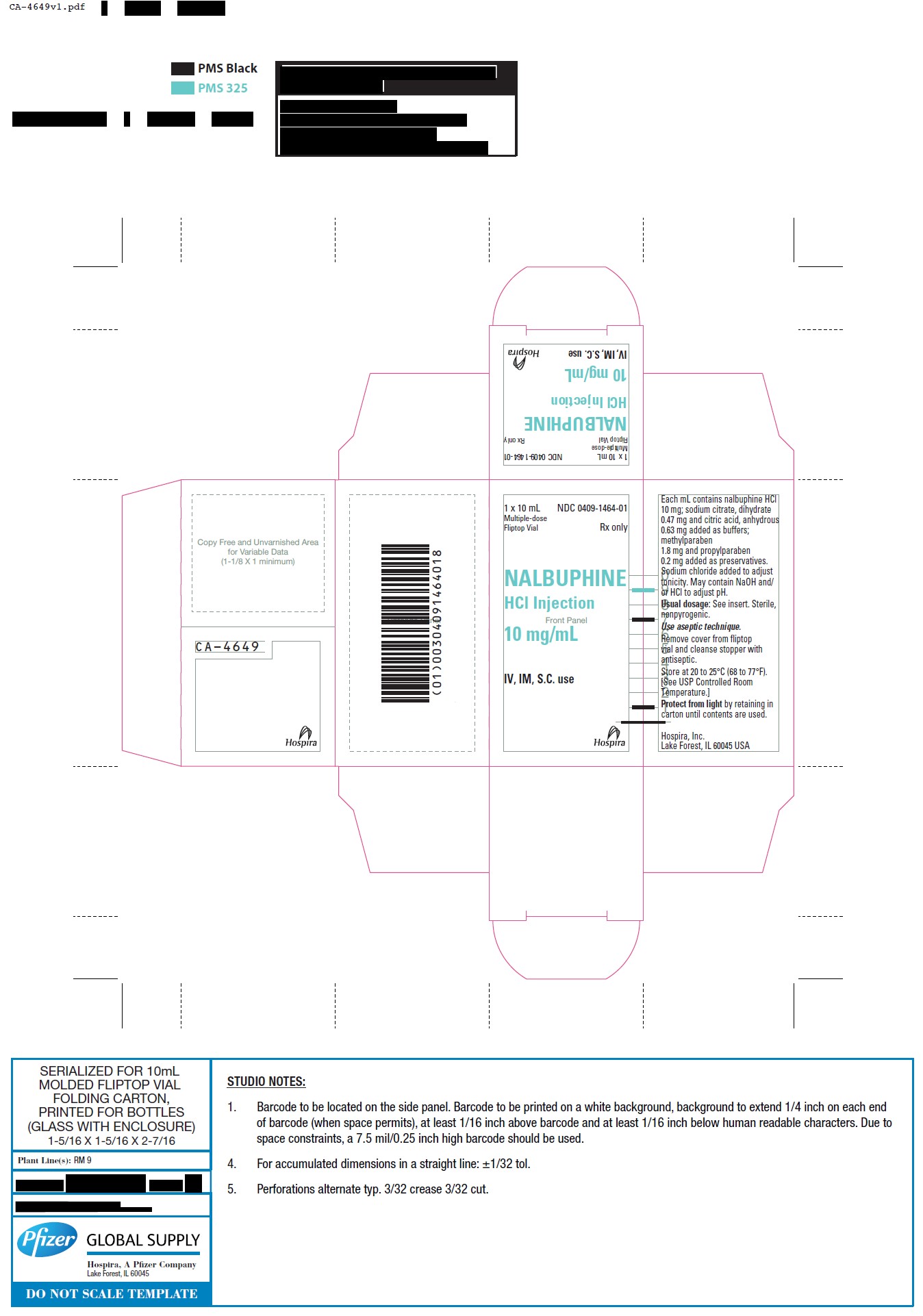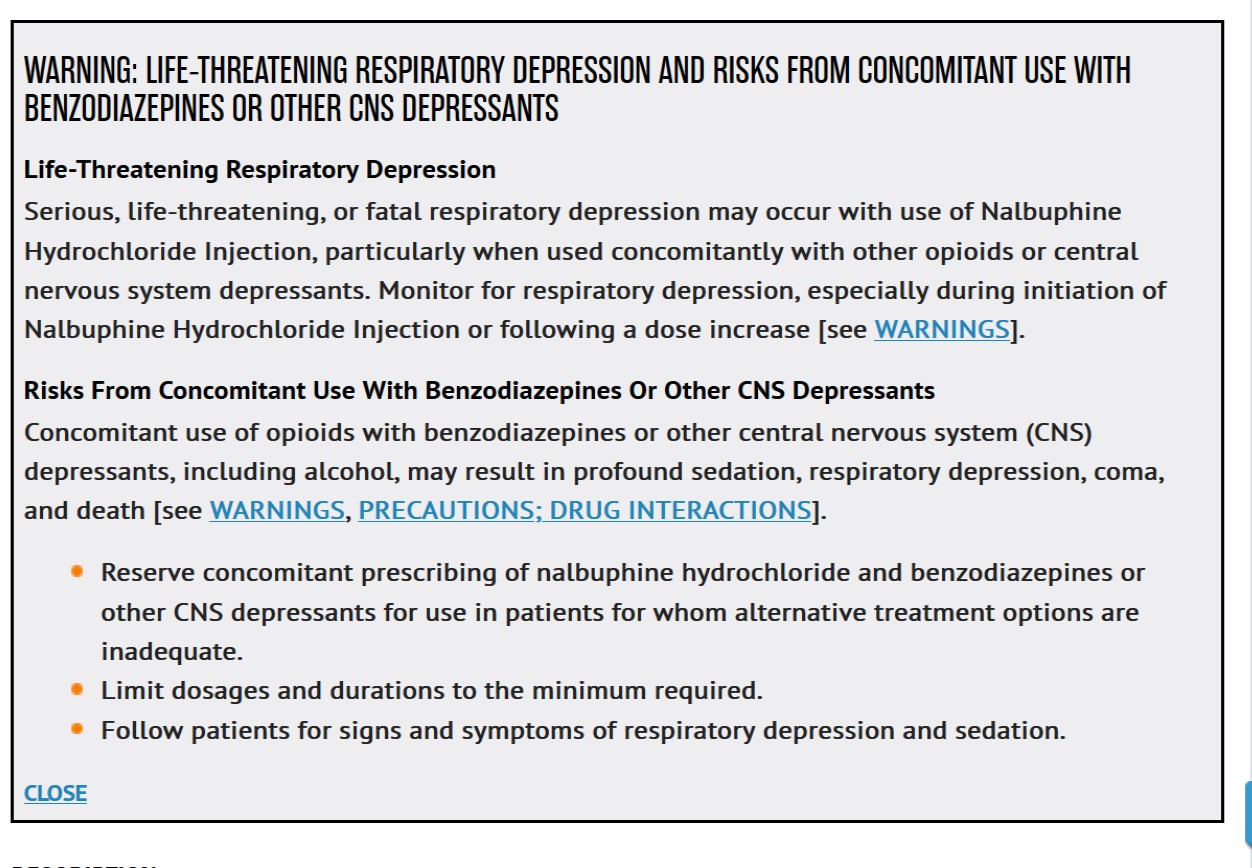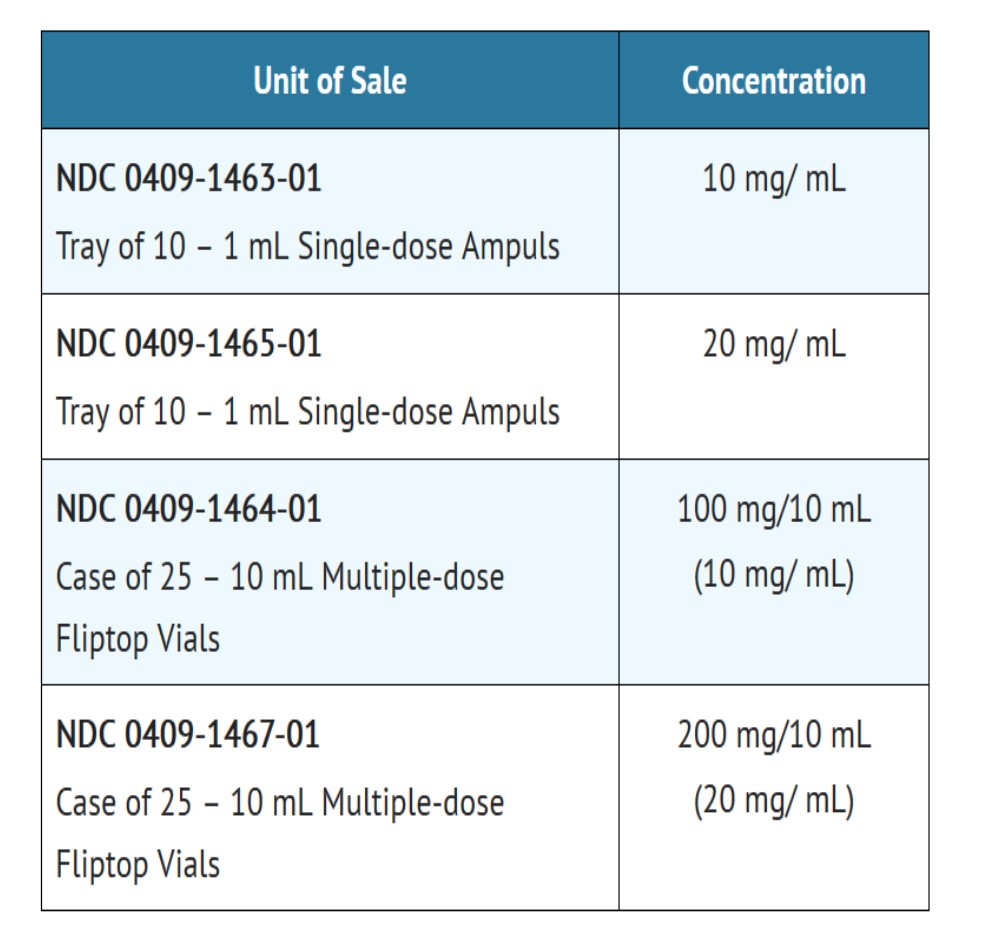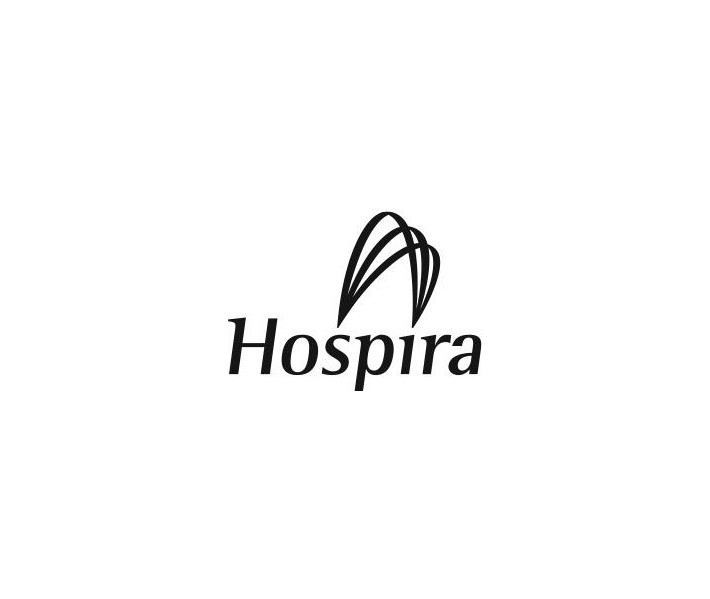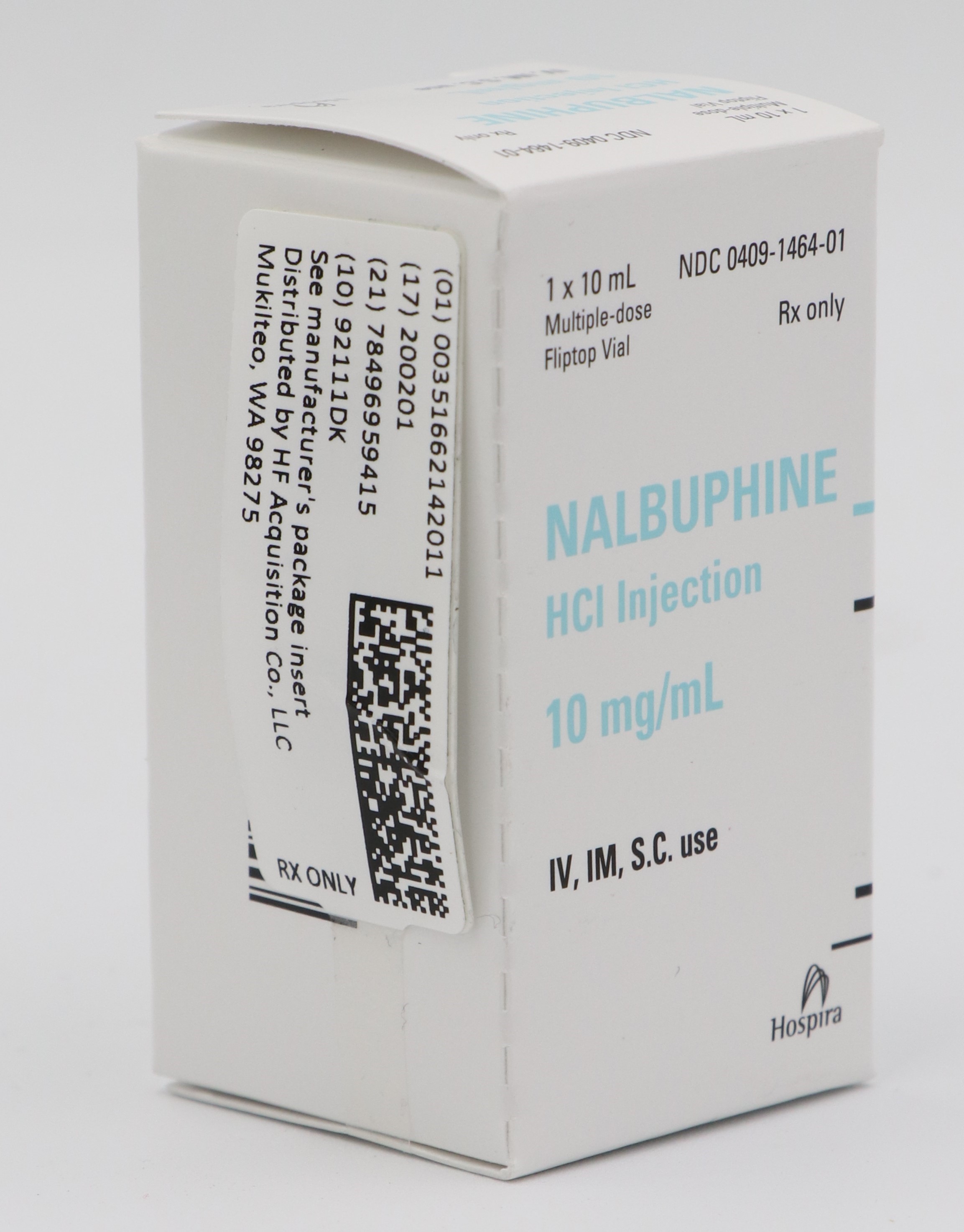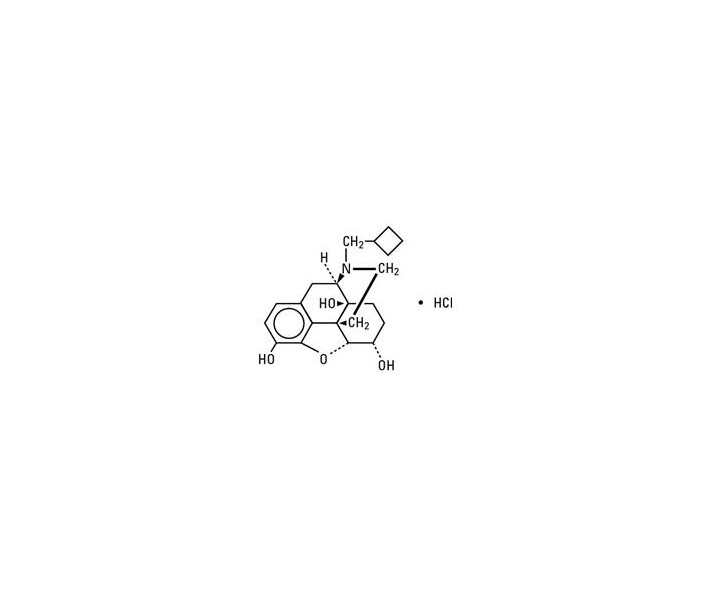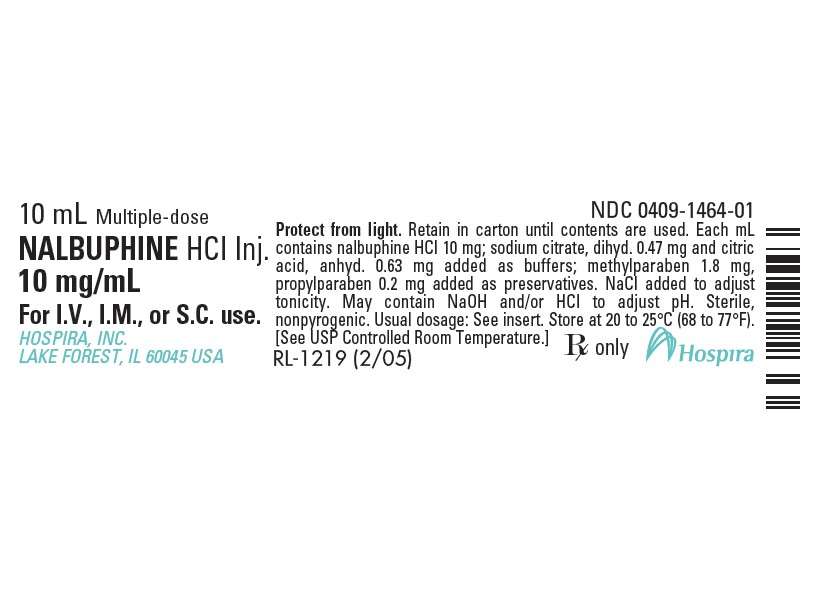 DRUG LABEL: NALBUPHINE HCI
NDC: 51662-1420 | Form: INJECTION, SOLUTION
Manufacturer: HF Acquisition Co LLC, DBA HealthFirst
Category: prescription | Type: HUMAN PRESCRIPTION DRUG LABEL
Date: 20250108

ACTIVE INGREDIENTS: NALBUPHINE HYDROCHLORIDE 10 mg/1 mL
INACTIVE INGREDIENTS: SODIUM CHLORIDE; HYDROCHLORIC ACID; METHYLPARABEN 1.8 mg/1 mL; WATER; TRISODIUM CITRATE DIHYDRATE 0.47 mg/1 mL; ANHYDROUS CITRIC ACID 0.63 mg/1 mL; SODIUM HYDROXIDE; PROPYLPARABEN 0.2 mg/1 mL

NALBUPHINE HCI INJ. 10mg/mL 10mL VIAL

SPL UNCLASSIFIED

Injection
Ampul
Fliptop Vial
Protect from light.

Rx only

BOXED WARNING

Life-Threatening Respiratory Depression - Serious, life-threatening, or fatal respiratory depression may occur with use of Nalbuphine Hydrochloride Injection, particularly when used concomitantly ...

DESCRIPTION

Nalbuphine hydrochloride is a synthetic opioid agonist-antagonist analgesic of the phenanthrene series. It is chemically related to both the widely used opioid antagonist, naloxone, and the potent opioid analgesic, oxymorphone. Chemically nalbuphine hydrochloride is 17-(cyclobutylmethyl)-4,5α-epoxymorphinan-3,6α,14-triol hydrochloride. Nalbuphine hydrochloride molecular weight is 393.91 and is soluble in H2O (35.5 mg/mL at 25°C) and ethanol (0.8%); insoluble in CHCl3 and ether. Nalbuphine hydrochloride has pKa values of 8.71 and 9.96. The molecular formula is C21H27NO4 ∙ HCl. The structural formula is:

Nalbuphine Hydrochloride Injection is a sterile, nonpyrogenic solution of nalbuphine hydrochloride in water for injection. This product may be administered by subcutaneous, intramuscular or intravenous injection.

Each milliliter (mL) contains nalbuphine hydrochloride 10 mg or 20 mg; sodium citrate, dihydrate 0.47 mg and citric acid, anhydrous 0.63 mg added as buffers and may contain sodium hydroxide and/or hydrochloric acid for pH adjustment; pH 3.7 (3.0 to 4.5). Contains sodium chloride for tonicity adjustment.

Multiple-dose vials contain 1.8 mg/mL methylparaben and 0.2 mg/mL propylparaben added as preservatives. Single-dose products contain no bacteriostat or antimicrobial agent and unused portions must be discarded.

CLINICAL PHARMACOLOGY

Effects on the Endocrine System

Chronic use of opioids may influence the hypothalamic-pituitary-gonadal axis, leading to androgen deficiency that may manifest as low libido, impotence, erectile dysfunction, amenorrhea, or infertility. The causal role of opioids in the clinical syndrome of hypogonadism is unknown because the various medical, physical, lifestyle, and psychological stressors that may influence gonadal hormone levels have not been adequately controlled for in studies conducted to date.

Nalbuphine Hydrochloride Injection is a potent analgesic. Its analgesic potency is essentially equivalent to that of morphine on a milligram basis. Receptor studies show that nalbuphine hydrochloride binds to mu, kappa, and delta receptors, but not to sigma receptors. Nalbuphine hydrochloride is primarily a kappa agonist/partial mu antagonist analgesic.

The onset of action of nalbuphine hydrochloride occurs within 2 to 3 minutes after intravenous administration, and in less than 15 minutes following subcutaneous or intramuscular injection. The plasma half-life of nalbuphine is 5 hours, and in clinical studies the duration of analgesic activity has been reported to range from 3 to 6 hours.

The opioid antagonist activity of nalbuphine hydrochloride is one-fourth as potent as nalorphine and 10 times that of pentazocine.

Nalbuphine hydrochloride may produce the same degree of respiratory depression as equianalgesic doses of morphine. However, Nalbuphine Hydrochloride Injection exhibits a ceiling effect such that increases in dose greater than 30 mg do not produce further respiratory depression in the absence of other CNS active medications affecting respiration.

Nalbuphine hydrochloride by itself has potent opioid antagonist activity at doses equal to or lower than its analgesic dose. When administered following or concurrent with mµ agonist opioid analgesics (e.g., morphine, oxymorphone, fentanyl), nalbuphine hydrochloride may partially reverse or block opioid-induced respiratory depression from the mµ agonist analgesic. Nalbuphine Hydrochloride Injection may precipitate withdrawal in patients dependent on opioid drugs. Nalbuphine Hydrochloride Injection should be used with caution in patients who have been receiving mu opioid analgesics on a regular basis.

INDICATIONS & USAGE

Nalbuphine Hydrochloride Injection is indicated for the management of pain severe enough to require an opioid analgesic and for which alternative treatments are inadequate. Nalbuphine Hydrochloride Injection can also be used as a supplement to balanced anesthesia, for preoperative and postoperative analgesia, and for obstetrical analgesia during labor and delivery.

Limitations of Use

Because of the risks of addiction, abuse, and misuse, with opioids, even at recommended doses [see WARNINGS], reserve Nalbuphine Hydrochloride Injection for use in patients for whom alternative treatment options [e.g., non-opioid analgesics]

Have not been tolerated, or are not expected to be tolerated
Have not provided adequate analgesia, or are not expected to provide adequate analgesia

CONTRAINDICATIONS

Nalbuphine Hydrochloride Injection is contraindicated in patients with:

Significant respiratory depression [see WARNINGS]
Acute or severe bronchial asthma in an unmonitored setting or in the absence of resuscitative equipment [see WARNINGS]
Known or suspected gastrointestinal obstruction, including paralytic ileus [see WARNINGS]
Hypersensitivity to nalbuphine or to any of the other ingredients in Nalbuphine Hydrochloride Injection.

WARNINGS

Life-Threatening Respiratory Depression

Serious, life-threatening, or fatal respiratory depression has been reported with the use of opioids, even when used as recommended. Respiratory depression, if not immediately recognized and treated, may lead to respiratory arrest and death. Management of respiratory depression may include close observation, supportive measures, and use of opioid antagonists, depending on the patient's clinical status [see OVERDOSAGE]. Carbon dioxide (CO2) retention from opioid-induced respiratory depression can exacerbate the sedating effects of opioids.

While serious, life-threatening, or fatal respiratory depression can occur at any time during the use of Nalbuphine Hydrochloride Injection, the risk is greatest during the initiation of therapy or following a dosage increase. Monitor patients closely for respiratory depression, especially within the first 24 to 72 hours of initiating therapy with and following dosage increases of Nalbuphine Hydrochloride Injection.

To reduce the risk of respiratory depression, proper dosing and titration of Nalbuphine Hydrochloride Injection is essential [see DOSAGE & ADMINISTRATION]. Overestimating the Nalbuphine Hydrochloride Injection dosage when converting patients from another opioid product can result in a fatal overdose with the first dose.

Opioids can cause sleep-related breathing disorders including central sleep apnea (CSA) and sleep-related hypoxemia. Opioid use increases the risk of CSA in a dose-dependent fashion. In patients who present with CSA, consider decreasing the opioid dosage using best practices for opioid taper [see DOSAGE & ADMINISTRATION].

Risks from Concomitant Use with Benzodiazepines or Other CNS Depressants

Profound sedation, respiratory depression, coma, and death may result from the concomitant use of Nalbuphine Hydrochloride Injection with benzodiazepines or other CNS depressants (e.g., non-benzodiazepine sedatives/hypnotics, anxiolytics, tranquilizers, muscle relaxants, general anesthetics, antipsychotics, other opioids, alcohol). Because of these risks, reserve concomitant prescribing of these drugs for use in patients for whom alternative treatment options are inadequate.

Observational studies have demonstrated that concomitant use of opioid analgesics and benzodiazepines increases the risk of drug-related mortality compared to use of opioid analgesics alone. Because of similar pharmacological properties, it is reasonable to expect similar risk with the concomitant use of other CNS depressant drugs with opioid analgesics [see PRECAUTIONS; Drug Interactions].

If the decision is made to prescribe a benzodiazepine or other CNS depressant concomitantly with an opioid analgesic, prescribe the lowest effective dosages and minimum durations of concomitant use. In patients already receiving an opioid analgesic, prescribe a lower initial dose of the benzodiazepine or other CNS depressant than indicated in the absence of an opioid, and titrate based on clinical response. If an opioid analgesic is initiated in a patient already taking a benzodiazepine or other CNS depressant, prescribe a lower initial dose of the opioid analgesic, and titrate based on clinical response. Follow patients closely for signs and symptoms of respiratory depression and sedation.

Advise both patients and caregivers about the risks of respiratory depression and sedation when Nalbuphine Hydrochloride Injection is used with benzodiazepines or other CNS depressants (including alcohol and illicit drugs). Advise patients not to drive or operate heavy machinery until the effects of concomitant use of the benzodiazepine or other CNS depressant have been determined. Screen patients for risk of substance use disorders, including opioid abuse and misuse, and warn them of the risk for overdose and death associated with the use of additional CNS depressants including alcohol and illicit drugs [see PRECAUTIONS; Drug Interactions and Information for Patients].

Life-Threatening Respiratory Depression in Patients with Chronic Pulmonary Disease or in Elderly, Cachectic, or Debilitated Patients

The use of Nalbuphine Hydrochloride Injection in patients with acute or severe bronchial asthma in an unmonitored setting or in the absence of resuscitative equipment is contraindicated.

Patients with Chronic Pulmonary Disease

Nalbuphine Hydrochloride Injection-treated patients with significant chronic obstructive pulmonary disease or cor pulmonale, and those with a substantially decreased respiratory reserve, hypoxia, hypercapnia, or pre-existing respiratory depression are at increased risk of decreased respiratory drive including apnea, even at recommended dosages of use of Nalbuphine Hydrochloride Injection [see WARNINGS].

Elderly, Cachectic, or Debilitated Patients

Life-threatening respiratory depression is more likely to occur in elderly, cachectic, or debilitated patients because they may have altered pharmacokinetics or altered clearance compared to younger, healthier patients [see WARNINGS]. Monitor such patients closely, particularly when initiating and titrating Nalbuphine Hydrochloride Injection and when Nalbuphine Hydrochloride Injection is given concomitantly with other drugs that depress respiration [see WARNINGS]. Alternatively, consider the use of non-opioid analgesics in these patients.

Adrenal Insufficiency

Cases of adrenal insufficiency have been reported with opioid use, more often following greater than 1 month of use. Presentation of adrenal insufficiency may include non-specific symptoms and signs including nausea, vomiting, anorexia, fatigue, weakness, dizziness, and low blood pressure. If adrenal insufficiency is suspected, confirm the diagnosis with diagnostic testing as soon as possible. If adrenal insufficiency is diagnosed, treat with physiologic replacement doses of corticosteroids. Wean the patient off of the opioid to allow adrenal function to recover and continue corticosteroid treatment until adrenal function recovers. Other opioids may be tried as some cases reported use of a different opioid without recurrence of adrenal insufficiency. The information available does not identify any particular opioids as being more likely to be associated with adrenal insufficiency.

Head Injury and Increased Intracranial Pressure

The possible respiratory depressant effects and the potential of potent analgesics to elevate cerebrospinal fluid pressure (resulting from vasodilation following CO2 retention) may be markedly exaggerated in the presence of head injury, intracranial lesions or a pre-existing increase in intracranial pressure. Furthermore, potent analgesics can produce effects which may obscure the clinical course of patients with head injuries. Therefore, Nalbuphine Hydrochloride Injection should be used in these circumstances only when essential, and then should be administered with extreme caution.

Use in Ambulatory Patients

Nalbuphine Hydrochloride Injection may impair the mental or physical abilities required for the performance of potentially dangerous tasks such as driving a car or operating machinery. Therefore, Nalbuphine Hydrochloride Injection should be administered with caution to ambulatory patients who should be warned to avoid such hazards.

Use in Emergency Procedures

Maintain patient under observation until recovered from Nalbuphine Hydrochloride Injection effects that would affect driving or other potentially dangerous tasks.

Use in Pregnancy (Other Than Labor)

Severe fetal bradycardia has been reported when Nalbuphine Hydrochloride Injection is administered during labor. Naloxone may reverse these effects. Although there are no reports of fetal bradycardia earlier in pregnancy, it is possible that this may occur. Avoid the use of Nalbuphine Hydrochloride Injection in pregnant women unless the potential benefit outweighs the risk to the fetus, and if appropriate measures such as fetal monitoring are taken to detect and manage any potential adverse effect on the fetus.

Use During Labor and Delivery

The placental transfer of nalbuphine is high, rapid, and variable with a maternal to fetal ratio ranging from 1:0.37 to 1:6. Fetal and neonatal adverse effects that have been reported following the administration of nalbuphine to the mother during labor include fetal bradycardia, respiratory depression at birth, apnea, cyanosis, and hypotonia. Some of these events have been life-threatening. Maternal administration of naloxone during labor has normalized these effects in some cases. Severe and prolonged fetal bradycardia has been reported. Permanent neurological damage attributed to fetal bradycardia has occurred. A sinusoidal fetal heart rate pattern associated with the use of nalbuphine has also been reported. Nalbuphine should be used during labor and delivery only if clearly indicated and only if the potential benefit outweighs the risk to the infant. Newborns should be monitored for respiratory depression, apnea, bradycardia and arrhythmias if nalbuphine has been used.

Addiction, Abuse, and Misuse

Nalbuphine hydrochloride is a synthetic opioid agonist-antagonist analgesic. As an opioid, Nalbuphine Hydrochloride Injection exposes users to the risks of addiction, abuse, and misuse [see DRUG ABUSE AND DEPENDENCE].

Although the risk of addiction in any individual is unknown, it can occur in patients appropriately prescribed Nalbuphine Hydrochloride Injection. Addiction can occur at recommended dosages and if the drug is misused or abused.

Assess each patient's risk for opioid addiction, abuse, or misuse. Risks are increased in patients with a personal or family history of substance abuse (including drug or alcohol abuse or addiction) or mental illness (e.g., major depression). The potential for these risks should not, however, prevent the proper management of pain in any given patient.

Opioids are sought by drug abusers and people with addiction disorders and are subject to criminal diversion. Consider these risks when prescribing or dispensing Nalbuphine Hydrochloride Injection. Strategies to reduce these risks include prescribing the drug in the smallest appropriate quantity. Contact local state professional licensing board or state controlled substances authority for information on how to prevent and detect abuse or diversion of this product.

PRECAUTIONS

General

Impaired Renal or Hepatic Function

Because nalbuphine is metabolized in the liver and excreted by the kidneys, Nalbuphine Hydrochloride Injection should be used with caution in patients with renal or liver dysfunction and administered in reduced amounts.

Myocardial Infarction

As with all potent analgesics, Nalbuphine Hydrochloride Injection should be used with caution in patients with myocardial infarction who have nausea or vomiting.

Biliary Tract Surgery

As with all opioid analgesics, Nalbuphine Hydrochloride Injection should be used with caution in patients about to undergo surgery of the biliary tract since it may cause spasm of the sphincter of Oddi.

Cardiovascular System

During evaluation of Nalbuphine Hydrochloride Injection in anesthesia, a higher incidence of bradycardia has been reported in patients who did not receive atropine pre-operatively.

Information for Patients

Patients should be advised of the following information:

Serotonin Syndrome

Inform patients that opioids could cause a rare but potentially life-threatening condition resulting from concomitant administration of serotonergic drugs. Warn patients of the symptoms of serotonin syndrome and to seek medical attention right away if symptoms develop. Instruct patients to inform their physicians if they are taking, or plan to take serotonergic medications [see PRECAUTIONS; Drug Interactions].

Nalbuphine Hydrochloride Injection is associated with sedation and may impair mental and physical abilities required for the performance of potentially dangerous tasks such as driving a car or operating machinery.
Nalbuphine Hydrochloride Injection is to be used as prescribed by a physician. Dose or frequency should not be increased without first consulting with a physician since Nalbuphine Hydrochloride Injection may cause psychological or physical dependence.
The use of Nalbuphine Hydrochloride Injection with other opioids can cause signs and symptoms of withdrawal.
Abrupt discontinuation of Nalbuphine Hydrochloride Injection after prolonged usage may cause signs and symptoms of withdrawal.

Laboratory Tests

Nalbuphine Hydrochloride Injection may interfere with enzymatic methods for the detection of opioids depending on the specificity/sensitivity of the test. Consult the test manufacturer for specific details.

Drug Interactions

Benzodiazepines and other Central Nervous System (CNS) Depressants

Although Nalbuphine Hydrochloride Injection possesses opioid antagonist activity, there is evidence that in nondependent patients it will not antagonize an opioid analgesic administered just before, concurrently, or just after an injection of Nalbuphine Hydrochloride Injection. Therefore, due to additive pharmacologic effects, the concomitant use of other opioid analgesics, benzodiazepines or other CNS depressants such as alcohol, other sedatives/hypnotics, anxiolytics, tranquilizers, muscle relaxants, general anesthetics, antipsychotics, and other opioids, can increase the risk of respiratory depression, profound sedation, coma, and death.

Reserve concomitant prescribing of these drugs for use in patients for whom alternative treatment options are inadequate. Limit dosages and durations to the minimum required. Follow patients closely for signs of respiratory depression and sedation [see WARNINGS].

Serotonergic Drugs

The concomitant use of opioids with other drugs that affect the serotonergic neurotransmitter system, such as selective serotonin reuptake inhibitors (SSRIs), serotonin and norepinephrine reuptake inhibitors (SNRIs), tricyclic antidepressants (TCAs), triptans, 5-HT3 receptor antagonists, drugs that affect the serotonin neurotransmitter system (e.g., mirtazapine, trazodone, tramadol), certain muscle relaxants (i.e., cyclobenzaprine, metaxalone), and monoamine oxidase (MAO) inhibitors (those intended to treat psychiatric disorders and also others, such as linezolid and intravenous methylene blue), has resulted in serotonin syndrome [see PRECAUTIONS; Information for Patients].

If concomitant use is warranted, carefully observe the patient, particularly during treatment initiation and dose adjustment. Discontinue Nalbuphine Hydrochloride Injection if serotonin syndrome is suspected.

Monoamine Oxidase Inhibitors (MAOIs)

MAOI (e.g., phenelzine, tranylcypromine, linezolid) interactions with opioids may manifest as serotonin syndrome [see Drug Interactions] or opioid toxicity (e.g., respiratory depression, coma [see Warnings]).

The use of Nalbuphine Hydrochloride Injection is not recommended for patients taking MAOIs or within 14 days of stopping such treatment.

If urgent use of an opioid is necessary, use test doses and frequent titration of small doses to treat pain while closely monitoring blood pressure and signs and symptoms of CNS and respiratory depression.

Carcinogenesis, Mutagenesis, Impairment of Fertility

Carcinogenesis

Long term carcinogenicity studies were performed in rats (24 months) and mice (19 months) by oral administration at doses up to 200 mg/kg (1180 mg/m2) and 200 mg/kg (600 mg/m2) per day, respectively. There was no evidence of an increase in tumors in either species related to Nalbuphine Hydrochloride Injection administration. The maximum recommend human dose (MRHD) in a day is 160 mg subcutaneously, intramuscularly or intravenously, or approximately 100 mg/m2/day for a 60 kg subject.

Mutagenesis

Nalbuphine Hydrochloride Injection did not have mutagenic activity in the AMES test with four bacterial strains, in the Chinese Hamster Ovary HGPRT assays or in the Sister Chromatids Exchange Assay. However, Nalbuphine Hydrochloride Injection induced an increased frequency of mutation in the mouse lymphoma assay. Clastogenic activity was not observed in the mouse micronucleus test of the cytogenicity bone marrow assay in rats.

Impairment of Fertility

A reproduction study was performed in male and female rats at subcutaneous doses up to 56 mg/kg/day or 330 mg/m2/day. Nalbuphine Hydrochloride Injection did not affect either male or female fertility rats.

Pregnancy

Teratogenic Effects

Reproduction studies have been performed in rats by subcutaneous administration of nalbuphine up to 100 mg/kg/day, or 590 mg/m2/day which is approximately 6 times the MRHD, and in rabbits by intravenous administration of nalbuphine up to 32 mg/kg/day, or 378 mg/m2/day which is approximately 4 times the MRHD. The results did not reveal evidence of developmental toxicity, including teratogenicity, or harm to the fetus. There are, however, no adequate and well-controlled studies in pregnant women. Because animal reproduction studies are not always predictive of human response, this drug should be used during pregnancy only if clearly needed.

Non-teratogenic Effects

Neonatal body weight and survival rates were reduced at birth and during lactation when nalbuphine was subcutaneously administered to female and male rats prior to mating and throughout gestation and lactation or to pregnant rats during the last third of gestation and throughout lactation at doses approximately 4 times the maximum recommended human dose.

Fetal/Neonatal Adverse Reactions

Severe fetal bradycardia has been reported when nalbuphine hydrochloride is administered during labor. Naloxone may reverse these effects. Although there are no reports of fetal bradycardia earlier in pregnancy, it is possible that this may occur. This drug should be used in pregnancy only if clearly needed, if the potential benefit outweighs the risk to the fetus, and if appropriate measures such as fetal monitoring are taken to detect and manage any potential adverse effect on the fetus.

Labor or Delivery

Opioids cross the placenta and may produce respiratory depression and psycho-physiologic effects in neonates. An opioid antagonist, such as naloxone, must be available for reversal of opioid-induced respiratory depression in the neonate. Nalbuphine Hydrochloride Injection is not recommended for use in pregnant women during or immediately prior to labor, when other analgesic techniques are more appropriate. Opioid analgesics, including Nalbuphine Hydrochloride Injection, can prolong labor through actions which temporarily reduce the strength, duration, and frequency of uterine contractions. However, this effect is not consistent and may be offset by an increased rate of cervical dilation, which tends to shorten labor. Monitor neonates exposed to opioid analgesics during labor for signs of excess sedation and respiratory depression.

Nursing Mothers

Limited data suggest that Nalbuphine Hydrochloride Injection is excreted in maternal milk but only in a small amount (less than 1% of the administered dose) and with a clinically insignificant effect.

Infants exposed to Nalbuphine Hydrochloride Injection through breast milk should be monitored for excess sedation and respiratory depression. Withdrawal symptoms can occur in breastfed infants when maternal administration of an opioid analgesic is stopped, or when breast-feeding is stopped.

Pediatric Use

Safety and effectiveness in pediatric patients below the age of 18 years have not been established.

Geriatric Use

Elderly patients (aged 65 years or older) may have increased sensitivity to Nalbuphine Hydrochloride Injection. In general, use caution when selecting a dosage for an elderly patient, usually starting at the low end of the dosing range, reflecting the greater frequency of decreased hepatic, renal, or cardiac function and of concomitant disease or other drug therapy.

Respiratory depression is the chief risk for elderly patients treated with opioids, and has occurred after large initial doses were administered to patients who were not opioid-tolerant or when opioids were co-administered with other agents that depress respiration. Titrate the dosage of Nalbuphine Hydrochloride Injection slowly in geriatric patients [see WARNINGS].

ADVERSE REACTIONS

The most frequent adverse reaction in 1066 patients treated in clinical studies with Nalbuphine Hydrochloride Injection was sedation 381 (36%).

Less frequent reactions were: sweaty/clammy 99 (9%), nausea/vomiting 68 (6%), dizziness/vertigo 58 (5%), dry mouth 44 (4%), and headache 27 (3%).

Other adverse reactions which occurred (reported incidence of 1% or less) were:

CNS Effects: Nervousness, depression, restlessness, crying, euphoria, floating, hostility, unusual dreams, confusion, faintness, hallucinations, dysphoria, feeling of heaviness, numbness, tingling, unreality. The incidence of psychotomimetic effects, such as unreality, depersonalization, delusions, dysphoria and hallucinations has been shown to be less than that which occurs with pentazocine.

Cardiovascular: Hypertension, hypotension, bradycardia, tachycardia.

Gastrointestinal: Cramps, dyspepsia, bitter taste.

Respiratory: Depression, dyspnea, asthma.

Dermatologic: Itching, burning, urticaria.

Miscellaneous: Speech difficulty, urinary urgency, blurred vision, flushing and warmth.

Allergic Reactions: Anaphylactic/anaphylactoid and other serious hypersensitivity reactions have been reported following the use of nalbuphine and may require immediate, supportive medical treatment. These reactions may include shock, respiratory distress, respiratory arrest, bradycardia, cardiac arrest, hypotension, or laryngeal edema. Some of these allergic reactions may be life-threatening. Other allergic-type reactions reported include stridor, bronchospasm, wheezing, edema, rash, pruritus, nausea, vomiting, diaphoresis, weakness, and shakiness.

Events Observed during Post-marketing Surveillance of Nalbuphine Hydrochloride Injection

Due to the nature and limitations of spontaneous reporting, causality has not been established for the following adverse events received for Nalbuphine Hydrochloride Injection: abdominal pain, pyrexia, depressed level or loss of consciousness, somnolence, tremor, anxiety, pulmonary edema, agitation, seizures, and injection site reactions such as pain, swelling, redness, burning, and hot sensations. Death has been reported from severe allergic reactions to Nalbuphine Hydrochloride Injection treatment. Fetal death has been reported where mothers received Nalbuphine Hydrochloride Injection during labor and delivery.

Serotonin syndrome: Cases of serotonin syndrome, a potentially life-threatening condition, have been reported during concomitant use of opioids with serotonergic drugs.

Adrenal insufficiency: Cases of adrenal insufficiency have been reported with opioid use, more often following greater than one month of use.

DRUG ABUSE AND DEPENDENCE

Abuse

Nalbuphine Hydrochloride Injection contains nalbuphine, which can be abused and is subject to misuse, addiction, and criminal diversion [see WARNINGS].

All patients treated with opioids require careful monitoring for signs of abuse and addiction, since use of opioid analgesic products carries the risk of addiction even under appropriate medical use.

Prescription drug abuse is the intentional non-therapeutic use of a prescription drug, even once, for its rewarding psychological or physiological effects.

Drug addiction is a cluster of behavioral, cognitive, and physiological phenomena that develop after repeated substance use and includes: a strong desire to take the drug, difficulties in controlling its use, persisting in its use despite harmful consequences, a higher priority given to drug use than to other activities and obligations, increased tolerance, and sometimes a physical withdrawal.

"Drug-seeking" behavior is very common in persons with substance use disorders. Drug-seeking tactics include emergency calls or visits near the end of office hours, refusal to undergo appropriate examination, testing, or referral, repeated "loss" of prescriptions, tampering with prescriptions, and reluctance to provide prior medical records or contact information for other treating health care provider(s). "Doctor shopping" (visiting multiple prescribers to obtain additional prescriptions) is common among drug abusers and people suffering from untreated addiction. Preoccupation with achieving adequate pain relief can be appropriate behavior in a patient with poor pain control.

Abuse and addiction are separate and distinct from physical dependence and tolerance. Health care providers should be aware that addiction may not be accompanied by concurrent tolerance and symptoms of physical dependence in all addicts. In addition, abuse of opioids can occur in the absence of true addiction.

Nalbuphine Hydrochloride Injection, like other opioids, can be diverted for non-medical use into illicit channels of distribution. Careful record-keeping of prescribing information, including quantity, frequency, and renewal requests, as required by state and federal law, is strongly advised.

Proper assessment of the patient, proper prescribing practices, periodic re-evaluation of therapy, and proper dispensing and storage are appropriate measures that help to limit abuse of opioid drugs.

Risks Specific to Abuse of Nalbuphine Hydrochloride

Abuse of Nalbuphine Hydrochloride Injection poses a risk of overdose and death. The risk is increased with concurrent abuse of Nalbuphine Hydrochloride Injection with alcohol and other central nervous system depressants.

Parenteral drug abuse is commonly associated with transmission of infectious diseases such as hepatitis and HIV.

Dependence

Both tolerance and physical dependence opioid therapy can develop during chronic opioid therapy. Tolerance is the need for increasing doses of opioids to maintain a defined effect such as analgesia (in the absence of disease progression or other external factors). Tolerance may occur to both the desired and undesired effects of drugs, and may develop at different rates for different effects.

Physical dependence results in withdrawal symptoms after abrupt discontinuation or a significant dosage reduction of a drug. Withdrawal also may be precipitated through the administration of drugs with opioid antagonist activity (e.g., naloxone, nalmefene), mixed agonist/antagonist analgesics (pentazocine, butorphanol, nalbuphine), or partial agonists (buprenorphine). Physical dependence may not occur to a clinically significant degree until after several days to weeks of continued opioid usage.

Nalbuphine Hydrochloride Injection should not be abruptly discontinued [see DOSAGE & ADMINISTRATION]. If Nalbuphine Hydrochloride Injection is abruptly discontinued in a physically-dependent patient, a withdrawal syndrome may occur. Some or all of the following can characterize this syndrome: restlessness, lacrimation, rhinorrhea, yawning, perspiration, chills, myalgia, and mydriasis. Other signs and symptoms also may develop, including: irritability, anxiety, backache, joint pain, weakness, abdominal cramps, insomnia, nausea, anorexia, vomiting, diarrhea, or increased blood pressure, respiratory rate, or heart rate.

Infants born to mothers physically dependent on opioids will also be physically dependent and may exhibit respiratory difficulties and withdrawal signs [see PRECAUTIONS; Pregnancy].

OVERDOSAGE

Clinical Presentation

Acute overdose with Nalbuphine Hydrochloride Injection alone can be manifested by respiratory depression and dysphoria. Acute overdose with Nalbuphine Hydrochloride Injection and other opioids or CNS depressants can be manifested by respiratory depression, somnolence progressing to stupor or coma, skeletal muscle flaccidity, cold and clammy skin, constricted pupils, and, in some cases, pulmonary edema, bradycardia, hypotension, partial or complete airway obstruction, atypical snoring, and death. Marked mydriasis rather than miosis may be seen with hypoxia in overdose situations.

Treatment of Overdose

In case of overdose, priorities are the reestablishment of a patent and protected airway and institution of assisted or controlled ventilation, if needed. Employ other supportive measures (including oxygen and vasopressors) in the management of circulatory shock and pulmonary edema as indicated. Cardiac arrest or arrhythmias will require advanced life-support techniques.

The opioid antagonists, naloxone or nalmefene, are specific antidotes to respiratory depression resulting from opioid overdose. For clinically significant respiratory or circulatory depression secondary to nalbuphine hydrochloride overdose, administer an opioid antagonist. Opioid antagonists should not be administered in the absence of clinically significant respiratory or circulatory depression secondary to Nalbuphine Hydrochloride Injection overdose.

Because the duration of opioid reversal is expected to be less than the duration of action of nalbuphine, carefully monitor the patient until spontaneous respiration is reliably re-established. If the response to an opioid antagonist is suboptimal or only brief in nature, administer additional antagonist as directed by the product's prescribing information.

In an individual physically dependent on opioids, administration of the recommended usual dosage of the antagonist will precipitate an acute withdrawal syndrome. The severity of the withdrawal symptoms experienced will depend on the degree of physical dependence and the dose of the antagonist administered. If a decision is made to treat serious respiratory depression in the physically dependent patient, administration of the antagonist should be initiated with care and by titration with smaller than usual doses of the antagonist.

DOSAGE & ADMINISTRATION

Important Dosage and Administration Instructions

Nalbuphine Hydrochloride Injection should be administered as a supplement to general anesthesia only by persons specifically trained in the use of intravenous anesthetics and management of the respiratory effects of potent opioids.

Naloxone, resuscitative and intubation equipment and oxygen should be readily available.

Initiate the dosing regimen for each patient individually, taking into account the patient's severity of pain, patient response, prior analgesic treatment experience, and risk factors for addiction, abuse, and misuse [see WARNINGS].

Monitor patients closely for respiratory depression, especially within the first 24 to 72 hours of initiating therapy and following dosage increases with Nalbuphine Hydrochloride Injection and adjust the dosage accordingly [see WARNINGS].

Parenteral drug products should be inspected visually for particulate matter and discoloration prior to administration whenever solution and container permit.

Initial Dosage

The usual recommended adult dose is 10 mg for a 70 kg individual administered subcutaneously, intramuscularly, or intravenously; this dose may be repeated every 3 to 6 hours as necessary. Dosage should be adjusted according to the severity of the pain, physical status of the patient, and other medications which the patient may be receiving [see WARNINGS; Risks from Concomitant Use with Benzodiazepines or Other CNS Depressants]. In nontolerant individuals, the recommended single maximum dose is 20 mg with a maximum total daily dose of 160 mg.

The use of Nalbuphine Hydrochloride Injection as a supplement to balanced anesthesia requires larger doses than those recommended for analgesia. Induction doses of nalbuphine hydrochloride range from 0.3 mg/kg to 3 mg/kg intravenously to be administered over a 10 to 15 minute period with maintenance doses of 0.25 to 0.5 mg/kg in single intravenous administrations as required. The use of Nalbuphine Hydrochloride Injection may be followed by respiratory depression which can be reversed with the opioid antagonist naloxone hydrochloride.

Titration and Maintenance of Therapy

Individually titrate Nalbuphine Hydrochloride Injection to a dose that provides adequate analgesia and minimizes adverse reactions. Continually reevaluate patients receiving nalbuphine hydrochloride to assess the maintenance of pain control and the relative incidence of adverse reactions, as well as monitoring for the development of addiction, abuse, or misuse [see WARNINGS]. Frequent communication is important among the prescriber, other members of the healthcare team, the patient, and the caregiver/family during periods of changing analgesic requirements, including initial titration.

If the level of pain increases after dosage stabilization, attempt to identify the source of increased pain before increasing the nalbuphine hydrochloride dosage. If unacceptable opioid-related adverse reactions are observed, consider reducing the dosage. Adjust the dosage to obtain an appropriate balance between management of pain and opioid-related adverse events.

Discontinuation of Nalbuphine Hydrochloride Injection

When a patient who has been taking Nalbuphine Hydrochloride Injection regularly and may be physically dependent no longer requires therapy with Nalbuphine Hydrochloride Injection, taper the dose gradually, by 25% to 50% every 2 to 4 days, while monitoring carefully for signs and symptoms of withdrawal. If the patient develops these signs or symptoms, raise the dose to the previous level and taper more slowly, either by increasing the interval between decreases, decreasing the amount of change in dose, or both. Do not abruptly discontinue Nalbuphine Hydrochloride Injection in a physically-dependent patient [see WARNINGS, DRUG ABUSE AND DEPENDENCE].

HOW SUPPLIED

NALBUPHINE HCI INJ. is supplied in the following dosage forms.
NDC 51662-1420-1
NALBUPHINE HCI INJ. 10mg/mL 10mL VIAL

HF Acquisition Co LLC, DBA HealthFirst
Mukilteo, WA 98275

Also supplied in the following manufacture supplied dosage forms

Nalbuphine Hydrochloride Injection for intramuscular, subcutaneous, or intravenous use is a sterile solution available in:

Store at 20 to 25°C (68 to 77°F). [See USP Controlled Room Temperature.]

Protect from excessive light. Store in carton until contents have been used.

SPL UNCLASSIFIED

Distributed by Hospira, Inc., Lake Forest, IL 60045 USA

LAB-0839-5.0

Revised: 06/2019